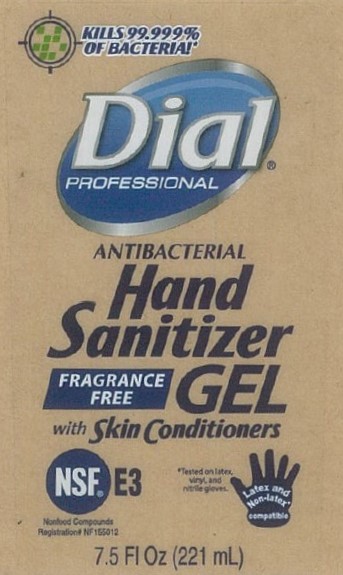 DRUG LABEL: Hand Sanitizer
NDC: 61531-389 | Form: GEL
Manufacturer: PakLab
Category: otc | Type: HUMAN OTC DRUG LABEL
Date: 20201130

ACTIVE INGREDIENTS: ALCOHOL 62 mL/100 mL
INACTIVE INGREDIENTS: GLYCERIN 0.5 mL/100 mL; 2-(1-CHLOROCYCLOPROPYL)-3-(2-CHLOROPHENYL)-1,2-PROPANEDIOL 0.5 mL/100 mL; WATER

Active Ingredient(s)

Ethyl Alcohol 62% v/v. Purpose: Antiseptic

Purpose

Antiseptic, Hand Sanitizer

Use

Hand Sanitizer to help reduce bacteria that potentially can cause disease.

Warnings

For external use only. Flammable. Keep away from heat or flame

When using this product avoid contact with face, eyes, and broken skin. If eyes contact occurs, flush thoroughly with water and seek medical advice.
Stop use and ask a doctor if irritation or rash occurs.
Keep out of reach of children. If swallowed, get medical help or contact a Poison Control Center right away.

Stop use and ask a doctor if irritation and redness develops.

Keep out of reach of children. If swallowed, get medical help or contact a Poison Control Center right away.

Directions

- Wet hand thoroughly with product and rub into skin until dry.
- Children under 6 years of age should be supervised by an adult when using this product.

Inactive ingredients

aqua (water, eau), propylene glycol, glycerin, carbomer, aminomethyl propanol, isopropyl myristate, t-butyl alcohol

Package Label - Principal Display Panel

221 mL NDC: 61531-389-01